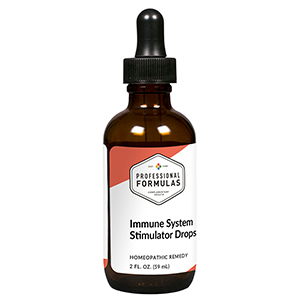 DRUG LABEL: Immune System Stimulator Drops
NDC: 63083-2033 | Form: LIQUID
Manufacturer: Professional Complementary Health Formulas
Category: homeopathic | Type: HUMAN OTC DRUG LABEL
Date: 20190815

ACTIVE INGREDIENTS: ECHINACEA ANGUSTIFOLIA WHOLE 2 [hp_X]/59 mL; SODIUM CHLORIDE 3 [hp_X]/59 mL; BERBERIS AQUIFOLIUM ROOT BARK 3 [hp_X]/59 mL; PETROSELINUM CRISPUM ROOT 3 [hp_X]/59 mL; SUS SCROFA LYMPH 6 [hp_X]/59 mL; SUS SCROFA COLON 6 [hp_X]/59 mL; BOS TAURUS BONE MARROW 6 [hp_X]/59 mL; BEEF LIVER 6 [hp_X]/59 mL; BOS TAURUS SPLEEN 6 [hp_X]/59 mL; HYSSOPUS OFFICINALIS WHOLE 6 [hp_X]/59 mL; BOS TAURUS TONSIL 6 [hp_X]/59 mL; SACCHARIN 50 [hp_X]/59 mL
INACTIVE INGREDIENTS: ALCOHOL; WATER

C33

ACTIVE INGREDIENTS

Echinacea angustifolia 2X
Aqua marina 3X
Berberis aquifolium 3X
Petroselinum sativum 3X
Adenoids 6X, 12X, 30X, 100X
Appendix 6X, 12X, 30X, 100X
Bone marrow 6X, 12X, 30X, 100X
Liver 6X, 12X, 30X, 100X
Spleen 6X, 12X, 30X, 100X
Thymus 6X, 12X, 30X, 100X
Tonsils 6X, 12X, 30X, 100X
Saccharinum 50X

QUESTIONS

Professional Formulas

PO Box 2034 Lake Oswego, OR 97035

INDICATIONS

For the temporary relief of sinus or nasal congestion, chills, minor aches or pains in muscles or joints, chills, occasional headache, or fatigue.*

PURPOSE

*Claims based on traditional homeopathic practice, not accepted medical evidence. Not FDA evaluated.

WARNINGS

Persistent symptoms may be a sign of a serious condition. If symptoms persist or are accompanied by a fever, rash, or persistent headache, consult a doctor. Keep out of the reach of children. In case of overdose, get medical help or contact a poison control center right away. If pregnant or breastfeeding, ask a healthcare professional before use.

Keep out of the reach of children.

PREGNANCY OR BREAST FEEDING

If pregnant or breastfeeding, ask a healthcare professional before use.

DIRECTIONS

Place drops under tongue 30 minutes before/after meals. Adults and children 12 years and over: Take 10 drops up to 3 times per day. Consult a physician for use in children under 12 years of age.

OTHER INFORMATION

Tamper resistant. If seal is broken, do not use. After opening, close container tightly and store at room temperature away from heat.

INACTIVE INGREDIENTS

20% ethanol, purified water.

LABEL

Est 1985

Professional Formulas

Complementary Health

Immune System Stimulator Drops

Homeopathic Remedy

2 FL. OZ. (59 mL)